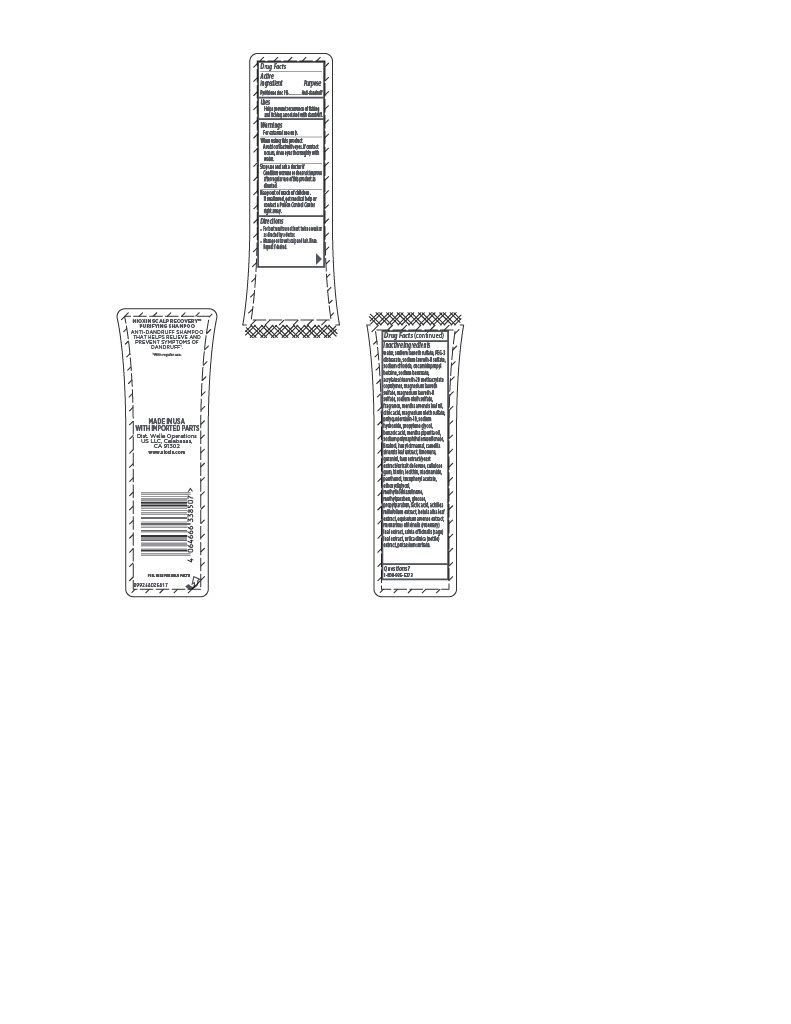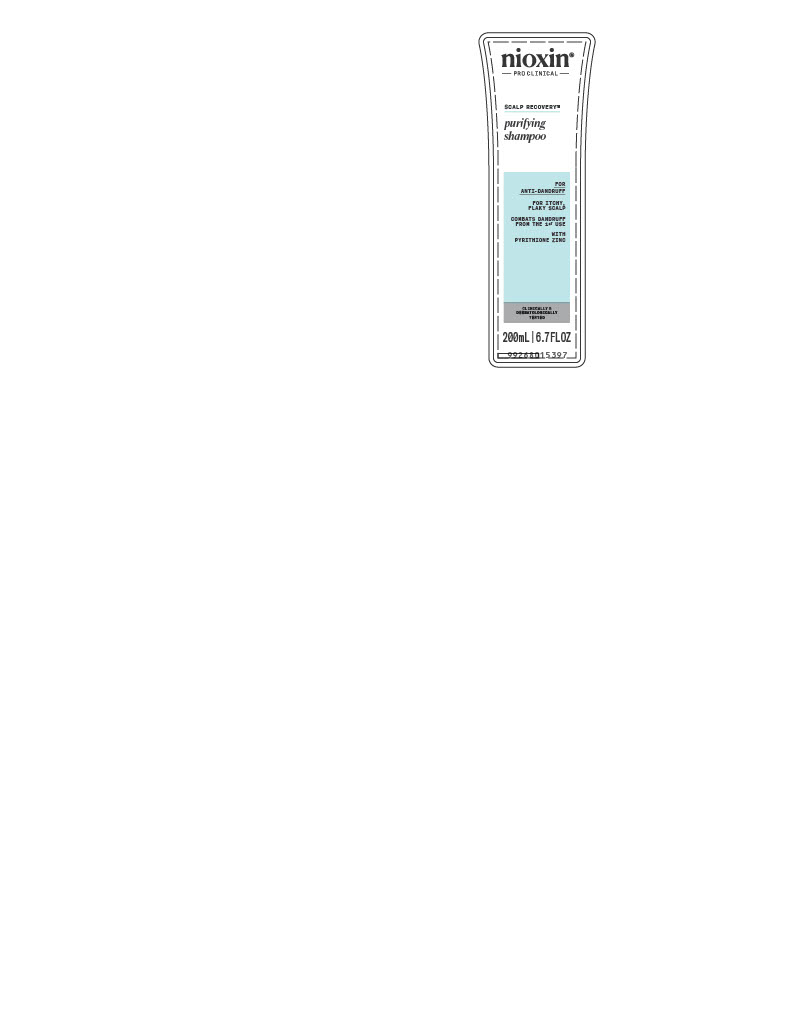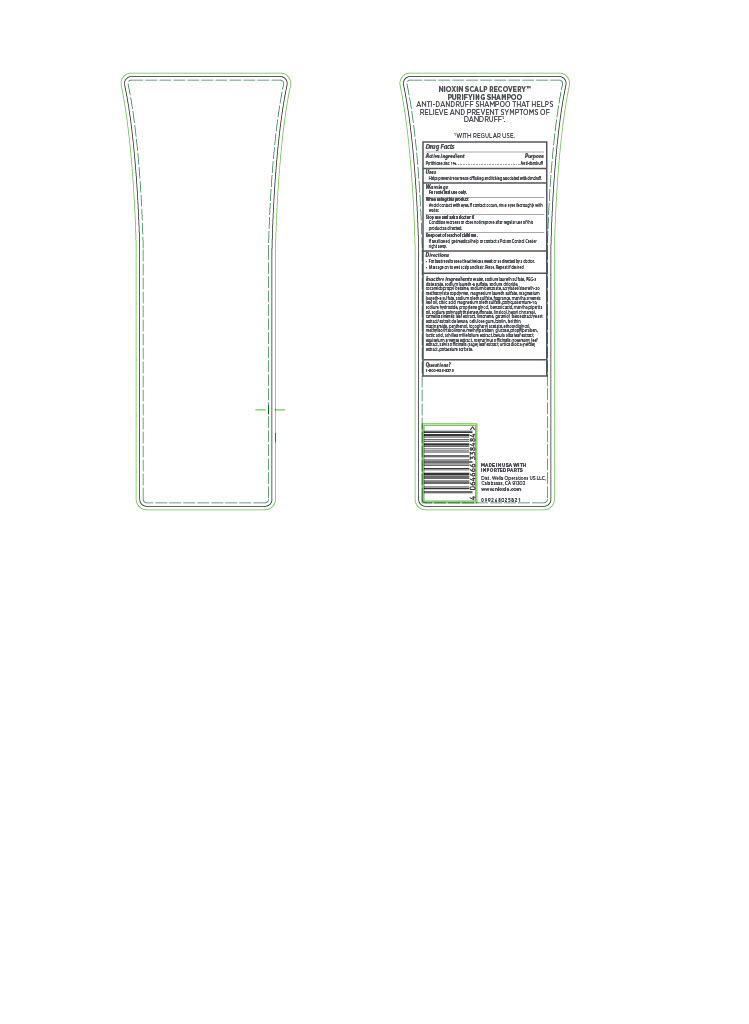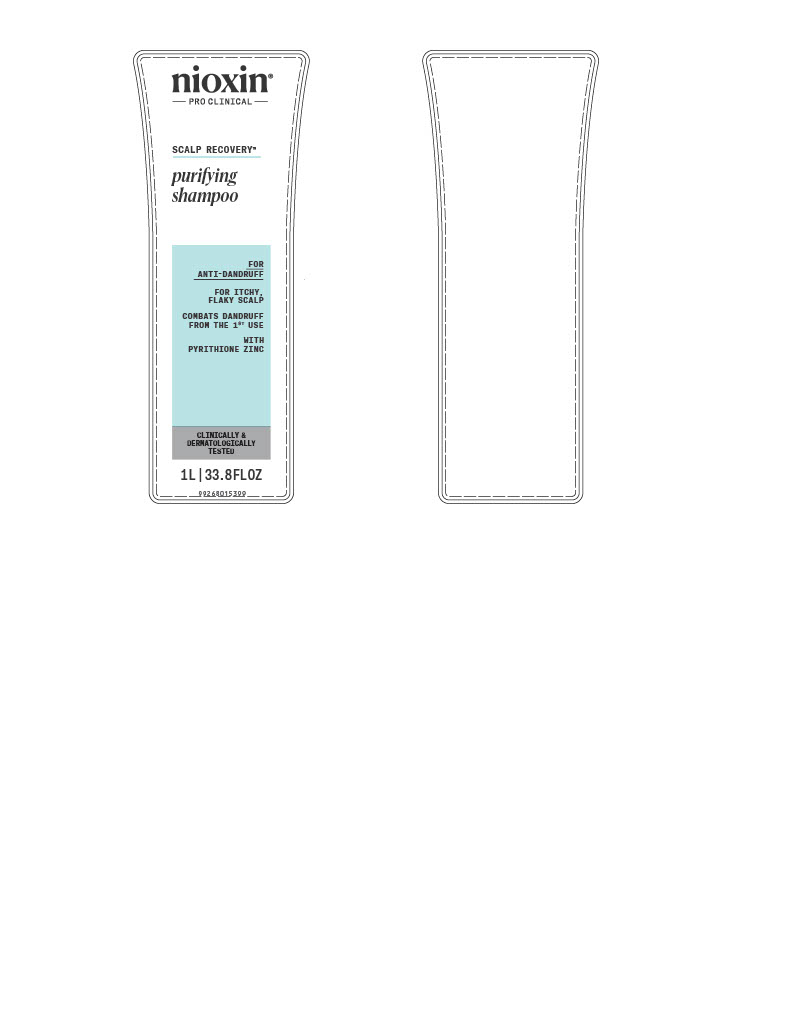 DRUG LABEL: Nioxin PRO CLINICAL SCALP RECOVERY purifying
NDC: 82157-011 | Form: SHAMPOO
Manufacturer: Wella Operations US LLC
Category: otc | Type: HUMAN OTC DRUG LABEL
Date: 20251125

ACTIVE INGREDIENTS: PYRITHIONE ZINC 1 g/100 mL
INACTIVE INGREDIENTS: SODIUM LAURETH-8 SULFATE; MENTHA ARVENSIS LEAF OIL; CITRIC ACID; MENTHA PIPERITA (PEPPERMINT) OIL; .ALPHA.-TOCOPHEROL ACETATE, D-; METHYLPARABEN; BETULA PUBESCENS LEAF; HEXYL CINNAMAL; WATER; POLYQUATERNIUM-10 (400 MPA.S AT 2%); YEAST, UNSPECIFIED; ETHOXYDIGLYCOL; ACHILLEA MILLEFOLIUM; BIOTIN; SODIUM HYDROXIDE; FORMALDEHYDE/SODIUM NAPHTHALENESULFONATE COPOLYMER (3000 MW); LINALOOL, (+/-)-; CAMELLIA SINENSIS LEAF; HEXAMETHYLINDANOPYRAN; GERANIOL; LECITHIN, SOYBEAN; PROPYLPARABEN; ROSEMARY; SAGE; URTICA DIOICA LEAF; POTASSIUM SORBATE; CALCIUM PANTOTHENATE; SODIUM CHLORIDE; INOSITOL; CELLULOSE GUM; NIACINAMIDE; EQUISETUM ARVENSE BRANCH; PANTHENOL; COCAMIDOPROPYL BETAINE; MAGNESIUM LAURETH SULFATE; SODIUM OLETH SULFATE; CARAMEL; TARTARIC ACID; MAGNESIUM LAURETH-8 SULFATE; ACRYLATES/STEARETH-20 METHACRYLATE COPOLYMER; SODIUM LAURETH SULFATE; PROPYLENE GLYCOL; BENZOIC ACID; PEG-3 DISTEARATE; SODIUM BENZOATE; LACTIC ACID; LIMONENE, (+/-)-; MAGNESIUM OLETH SULFATE; METHYLISOTHIAZOLINONE; GLUCOSE

nioxin PRO CLINICAL SCALP RECOVERY purifying shampoo

Drug Facts

Active Ingredient

Pyrithione zinc 1%

Purpose

Anti-dandruff

Uses

- Helps prevent recurrence of flaking and itching associated with dandruff.

Warnings

For external use only.

When using this product

- Avoid contact with eyes. If contact occurs, rinse eyes thoroughly with water.

Stop use and ask a doctor if

- Condition worsens or does not improve after regular use of this product as directed.

Keep out of reach of children. If swallowed, get medical help or contact a Poison Control Center right away.

Directions

- For best results use at least twice a week or as directed by a doctor.
- Massage on to wet scalp and hair. Rinse. Repeat if desired.

INACTIVE INGREDIENT

Inactive ingredients water, sodium laureth sulfate, PEG-3 distearate, sodium laureth-8 sulfate, sodium chloride, cocamidopropyl betaine, sodium benzoate, acrylates/steareth-20 methacrylate copolymer, magnesium laureth sulfate, magnesium laureth-8 sulfate, sodium oleth sulfate, fragrance, mentha arvensis leaf oil, citric acid, magnesium oleth sulfate, polyquaternium-10, sodium hydroxide, propylene glycol, benzoic acid, mentha piperita oil, sodium polynaphthalenesulfonate, linalool, hexyl cinnamal, camellia sinensis leaf extract, limonene, geraniol, faex extract/yeast extract/extrait de levure, cellulose gum, biotin, lecithin, niacinamide, panthenol, tocopheryl acetate, ethoxydiglycol, methylisothiazolinone, methylparaben, glucose, propylparaben, lactic acid, achillea millefolium extract, betula alba leaf extract, equisetum arvense extract, rosmarinus officinalis (rosemary) leaf extract, salvia officinalis (sage) leaf extract, urtica dioica (nettle) extract, potassium sorbate.

NIOXIN SCALP RECOVERY™

PURIFYING SHAMPOO

ANTI-DANDRUFF SHAMPOO THAT HELPS RELIEVE AND PREVENT SYMPTOMS OF DANDRUFF

WITH REGULAR USE

MADE IN USA WITH IMPORTED PARTS

Dist. Wella Operations US LLC, Calabasas, CA 91302

www.nioxin.com

Questions?

1-800-935-5273

PACKAGE LABEL

nioxin®

PRO CLINICAL

SCALP RECOVERY™

purifying shampoo

FOR ANTI-DANDRUFF

FOR ITCHY, FLAKY SCALP COMBATS DANDRUFF FROM THE 1ST USE WITH PYRITHIONE ZINC.

CLINICALLY & DERMATOLOGICALLY TESTED

200 mL | 6.7 FL OZ

nioxin®

PRO CLINICAL

SCALP RECOVERY™

purifying shampoo

FOR ANTI-DANDRUFF

FOR ITCHY, FLAKY SCALP COMBATS DANDRUFF FROM THE 1ST USE WITH PYRITHIONE ZINC.

CLINICALLY & DERMATOLOGICALLY TESTED

1L | 33.8 FL OZ